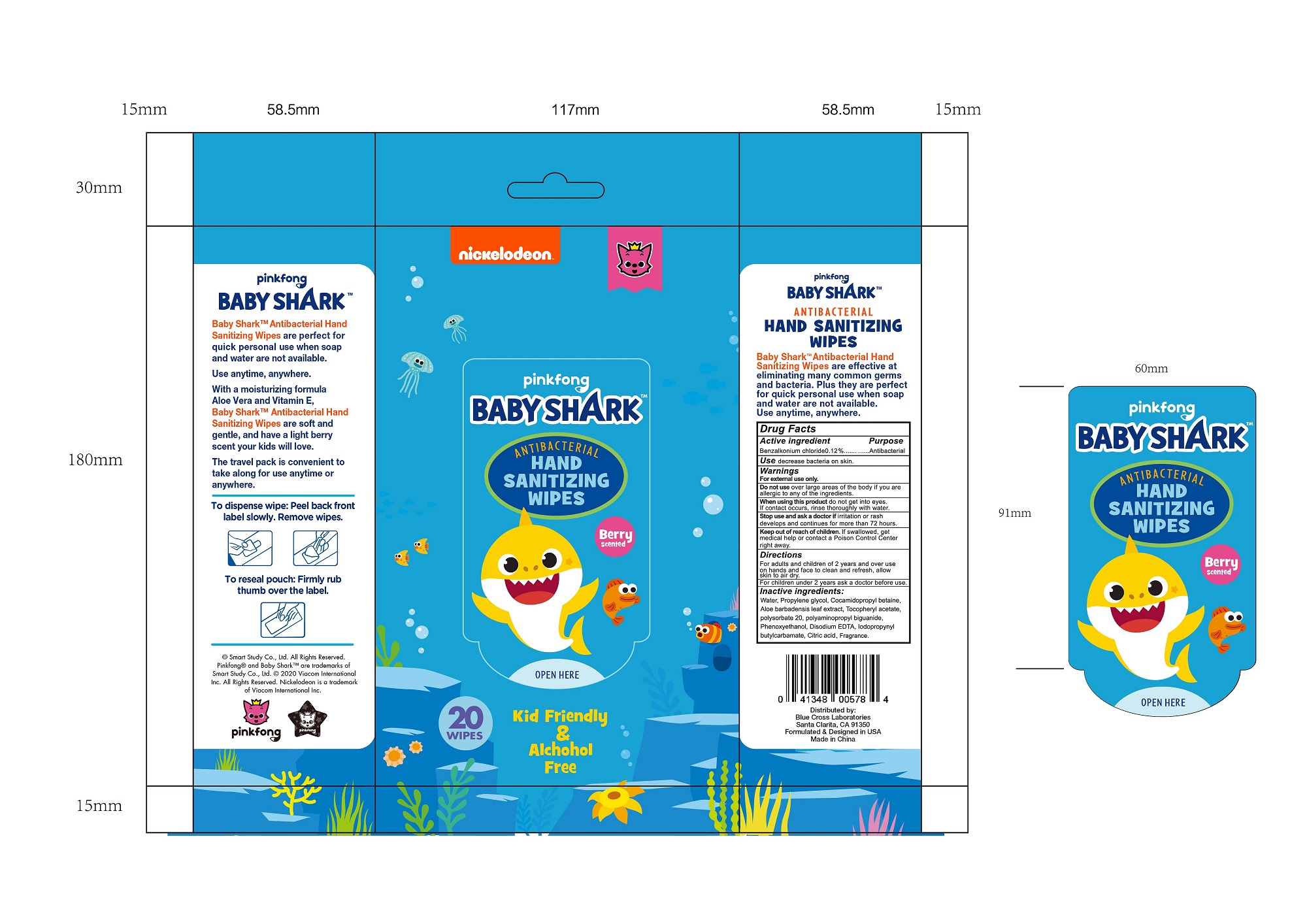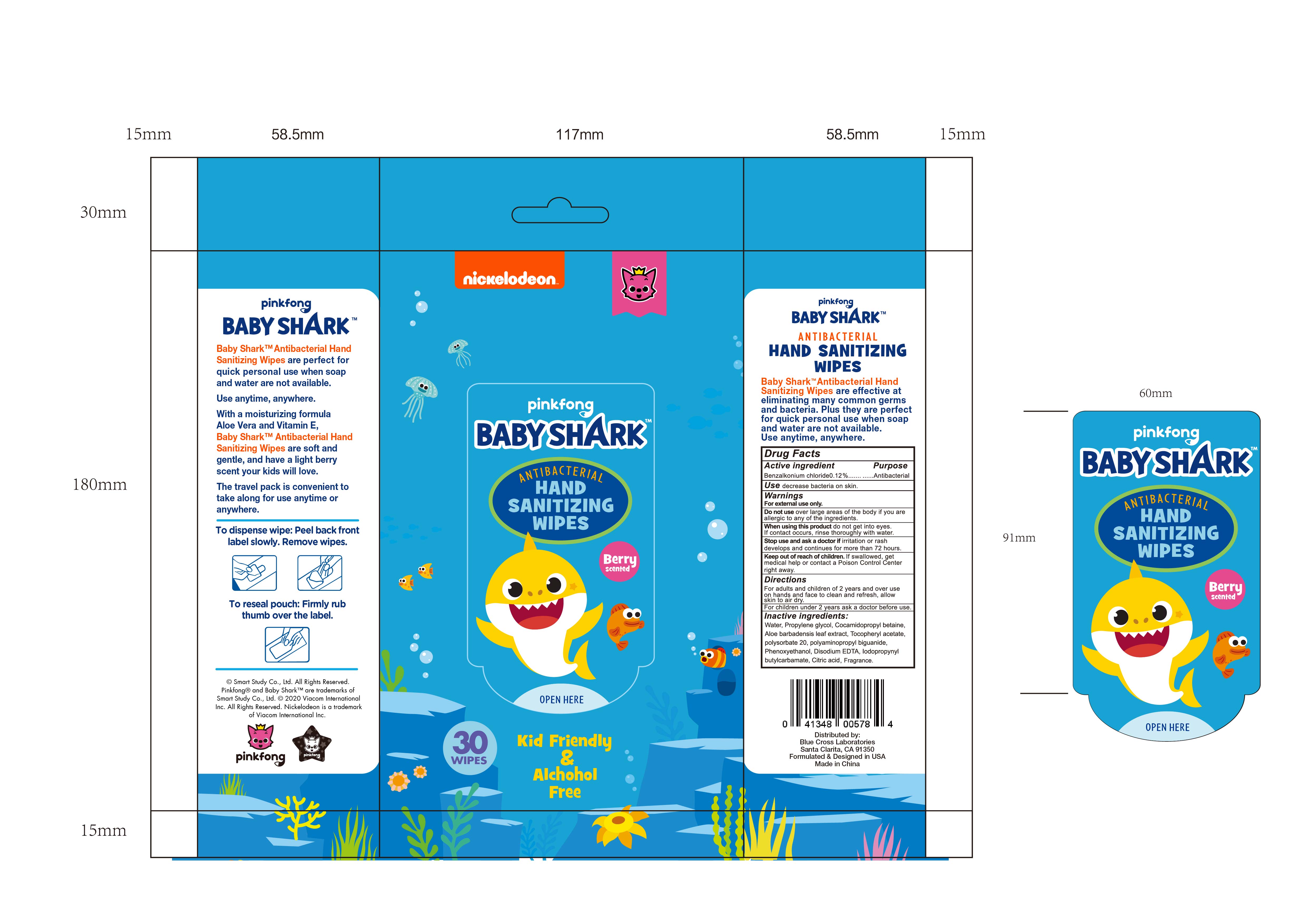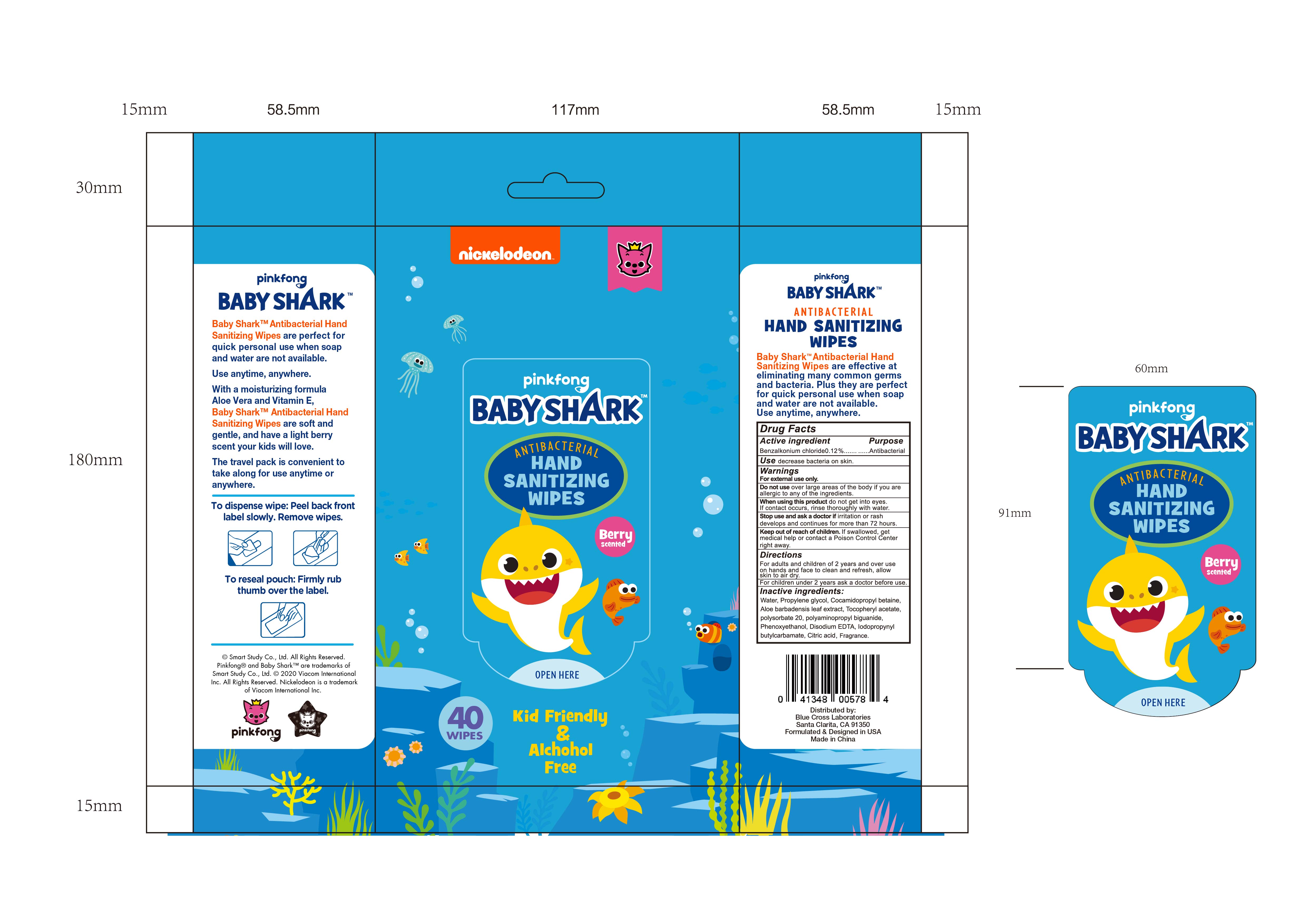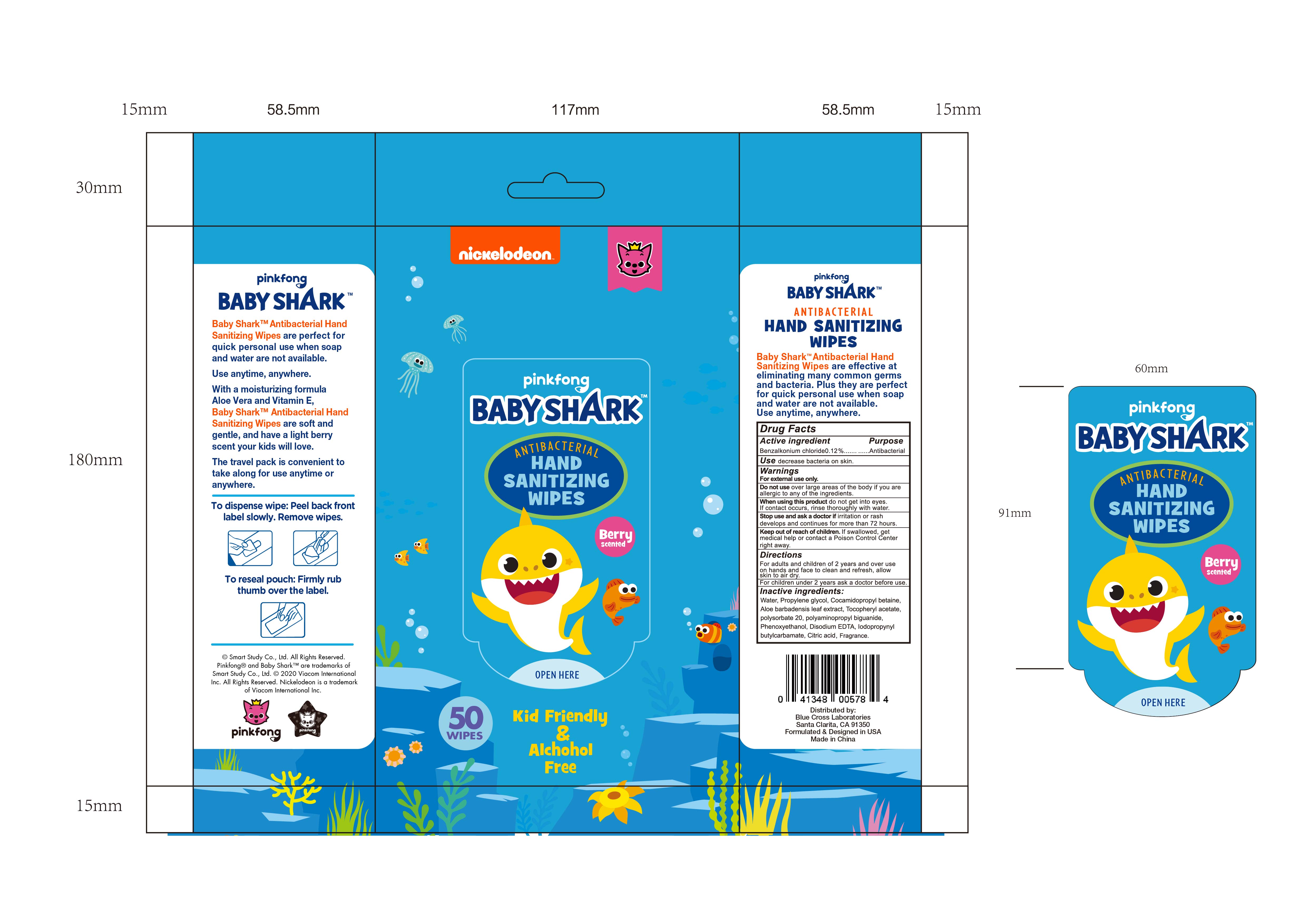 DRUG LABEL: BABY SHARK ANTIBACTERIAL HAND SANITIZING WIPES
NDC: 42255-902 | Form: CLOTH
Manufacturer: ZHEJIANG GREENFACE HOUSEWARES CO., LTD.
Category: otc | Type: HUMAN OTC DRUG LABEL
Date: 20200902

ACTIVE INGREDIENTS: BENZALKONIUM CHLORIDE 0.12 g/100 g
INACTIVE INGREDIENTS: IODOPROPYNYL BUTYLCARBAMATE; PHENOXYETHANOL; PROPYLENE GLYCOL; COCAMIDOPROPYL BETAINE; ALOE VERA LEAF; ALPHA-TOCOPHEROL ACETATE; WATER; POLYAMINOPROPYL BIGUANIDE; EDETATE DISODIUM ANHYDROUS; CITRIC ACID MONOHYDRATE; POLYSORBATE 20

42255-902 BABY SHARK ANTIBACTERIAL HAND SANITIZING WIPES 0.12% benzalkonium chloride

Active ingredient

Benzalkonium chloride 0.12%

Purpose

Antibacterial

Use

decreases bacteria on skin

Warnings

For external use only.

Do not use over large areas of the body

if you are allergic to any of the ingredients.

When using this product do not get into eyes.

If contact occurs, rinse thoroughly with water.

Stop use and ask a doctor if irritation or rash

develops and continues for more than 72 hours.
Keep out of reach of children.
If swallowed, get medical help or contact
a Poison Control Center right away.

Keep out of reach of children

if swallowed

get medical help or contact a Poison Control Center right away.

Directions

For adults and children of 2 years and over use

on hands and face to clean and refresh, allow

skin to air dry.

For children under 2 years ask a doctor before use.

INACTIVE INGREDIENT

Water, Propylene glycol, Cocamidopropyl betaine,
Aloe barbadensis leaf extract, Tocopheryl acetate,
Polysorbate 20, Polyaminopropyl biguanide,
Phenoxyethanol, Disodium EDTA, lodopropynyI
butylcarbamate, Citric acid.